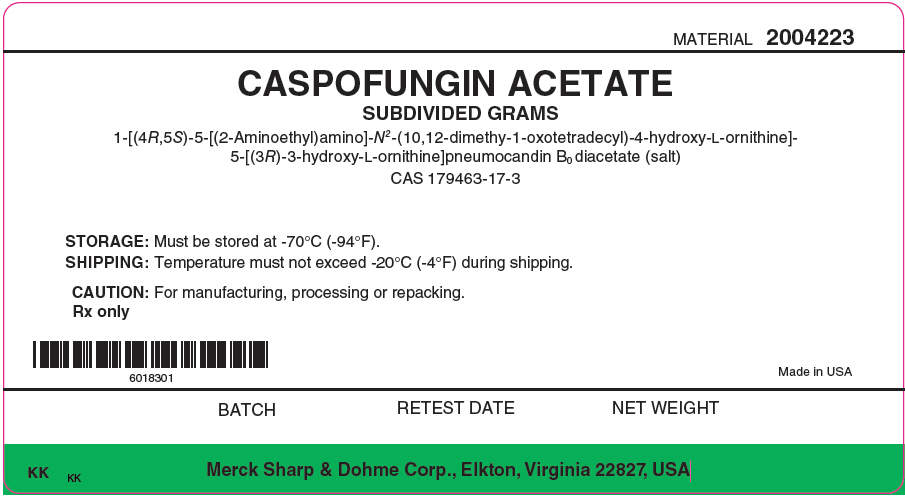 DRUG LABEL: CANCIDAS
NDC: 69806-0092 | Form: INJECTION, POWDER, LYOPHILIZED, FOR SOLUTION
Manufacturer: Merck Sharp & Dohme Corp.
Category: other | Type: BULK INGREDIENT
Date: 20221102

ACTIVE INGREDIENTS: CASPOFUNGIN ACETATE 1 kg/1 kg

CASPOFUNGIN ACETATE

PRINCIPAL DISPLAY PANEL - Shipping Label

MATERIAL 2004223

CASPOFUNGIN ACETATE
SUBDIVIDED GRAMS
1-[(4R,5S)-5-[(2-Aminoethyl)amino]-N^2-(10,12-dimethy-1-oxotetradecyl)-4-hydroxy-L-ornithine]-
5-[(3R)-3-hydroxy-L-ornithine]pneumocandin B0 diacetate (salt)
CAS 179463-17-3

STORAGE: Must be stored at -70°C (-94°F).

SHIPPING: Temperature must not exceed -20°C (-4°F) during shipping.

CAUTION: For manufacturing, processing or repacking.

Rx only

Made in USA

BATCH
RETEST DATE
NET WEIGHT

KK KK
Merck Sharp & Dohme Corp., Elkton, Virginia 22827, USA